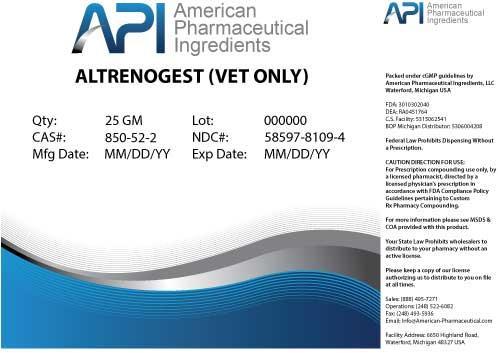 DRUG LABEL: ALTRENOGEST
NDC: 58597-8109 | Form: POWDER
Manufacturer: AMERICAN PHARMACEUTICAL INGREDIENTS LLC
Category: other | Type: BULK INGREDIENT
Date: 20140416

ACTIVE INGREDIENTS: ALTRENOGEST 1 g/1 g

ALTRENOGEST